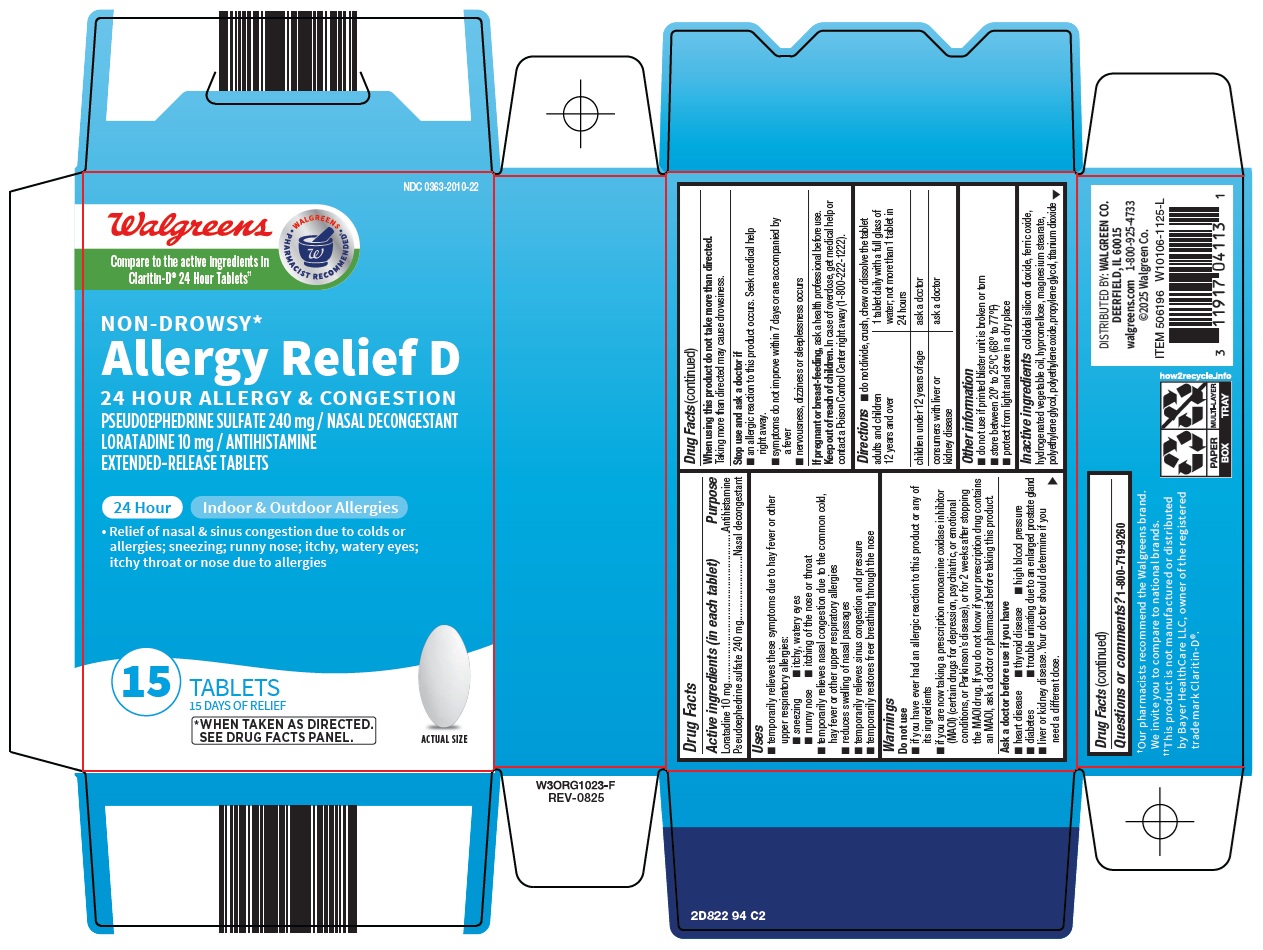 DRUG LABEL: Allergy Relief D
NDC: 0363-2010 | Form: TABLET, EXTENDED RELEASE
Manufacturer: Walgreen Company
Category: otc | Type: HUMAN OTC DRUG LABEL
Date: 20260228

ACTIVE INGREDIENTS: LORATADINE 10 mg/1 1; PSEUDOEPHEDRINE SULFATE 240 mg/1 1
INACTIVE INGREDIENTS: SILICON DIOXIDE; FERRIC OXIDE RED; HYPROMELLOSE, UNSPECIFIED; MAGNESIUM STEARATE; POLYETHYLENE GLYCOL, UNSPECIFIED; PROPYLENE GLYCOL; TITANIUM DIOXIDE

Walgreen Co. Allergy Relief D Drug Facts

Active ingredients (in each tablet)

Loratadine 10 mg

Pseudoephedrine sulfate 240 mg

Purpose

Antihistamine

Nasal decongestant

Uses

- temporarily relieves these symptoms due to hay fever or other upper respiratory allergies:
  - sneezing
  - itchy, watery eyes
  - runny nose
  - itching of the nose or throat
- temporarily relieves nasal congestion due to the common cold, hay fever or other upper respiratory allergies
- reduces swelling of nasal passages
- temporarily relieves sinus congestion and pressure
- temporarily restores freer breathing through the nose

Warnings

Do not use

- if you have ever had an allergic reaction to this product or any of its ingredients
- if you are now taking a prescription monoamine oxidase inhibitor (MAOI) (certain drugs for depression, psychiatric, or emotional conditions, or Parkinson’s disease), or for 2 weeks after stopping the MAOI drug. If you do not know if your prescription drug contains an MAOI, ask a doctor or pharmacist before taking this product.

Ask a doctor before use if you have

- heart disease
- thyroid disease
- high blood pressure
- diabetes
- trouble urinating due to an enlarged prostate gland
- liver or kidney disease. Your doctor should determine if you need a different dose.

When using this product do not take more than directed.

Taking more than directed may cause drowsiness.

Stop use and ask a doctor if

- an allergic reaction to this product occurs. Seek medical help right away.
- symptoms do not improve within 7 days or are accompanied by a fever
- nervousness, dizziness or sleeplessness occurs

If pregnant or breast-feeding,

ask a health professional before use.

Keep out of reach of children.

In case of overdose, get medical help or contact a Poison Control Center right away (1-800-222-1222).

Directions

- do not divide, crush, chew or dissolve the tablet

adults and children 12 years and over | 1 tablet daily with a full glass of water; not more than 1 tablet in 24 hours
children under 12 years of age | ask a doctor
consumers with liver or kidney disease | ask a doctor

Other information

- do not use if printed blister unit is broken or torn
- store between 20° to 25°C (68° to 77°F)
- protect from light and store in a dry place

Inactive ingredients

colloidal silicon dioxide, ferric oxide, hydrogenated vegetable oil, hypromellose, magnesium stearate, polyethylene glycol, polyethylene oxide, propylene glycol, titanium dioxide

Questions or comments?

1-800-719-9260

Package/Label Principal Display Panel

Walgreens

WALGREENS ● PHARMACIST RECOMMENDED ●

Compare to the active ingredients in Claritin-D® 24 Hour Tablets

NON-DROWSY*

Allergy Relief D

24 HOUR ALLERGY & CONGESTION

PSEUDOEPHEDRINE SULFATE 240 mg / NASAL DECONGESTANT

LORATADINE 10 mg / ANTIHISTAMINE

EXTENDED-RELEASE TABLETS

24 Hour

Indoor & Outdoor Allergies

• Relief of nasal & sinus congestion due to colds or allergies; sneezing; runny nose; itchy, watery eyes; itchy throat or nose due to allergies

15 TABLETS

15 DAYS OF RELIEF

*WHEN TAKEN AS DIRECTED. SEE DRUG FACTS PANEL.

ACTUAL SIZE